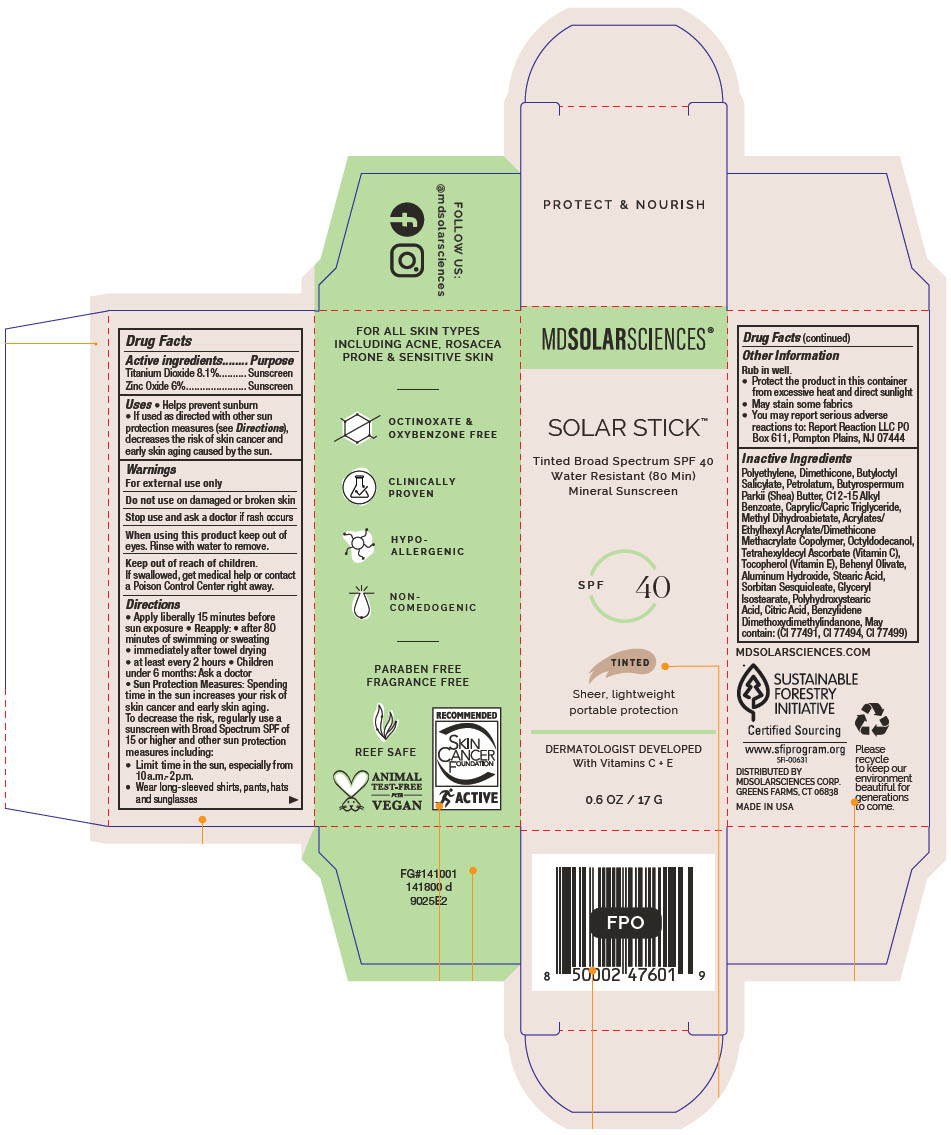 DRUG LABEL: Solar stick Tinted SPF 40
NDC: 49358-578 | Form: STICK
Manufacturer: MDSolarSciences
Category: otc | Type: HUMAN OTC DRUG LABEL
Date: 20250605

ACTIVE INGREDIENTS: TITANIUM DIOXIDE 81 mg/1 g; ZINC OXIDE 60 mg/1 g
INACTIVE INGREDIENTS: HIGH DENSITY POLYETHYLENE; DIMETHICONE; BUTYLOCTYL SALICYLATE; PETROLATUM; SHEA BUTTER; ALKYL (C12-15) BENZOATE; MEDIUM-CHAIN TRIGLYCERIDES; METHYL DIHYDROABIETATE; 2-ETHYLHEXYL ACRYLATE, METHACRYLATE, METHYL METHACRYLATE, OR BUTYL METHACRYLATE/HYDROXYPROPYL DIMETHICONE COPOLYMER (30000-300000 MW); OCTYLDODECANOL; TETRAHEXYLDECYL ASCORBATE; TOCOPHEROL; BEHENYL OLIVATE; ALUMINUM HYDROXIDE; STEARIC ACID; SORBITAN SESQUIOLEATE; GLYCERYL ISOSTEARATE; POLYHYDROXYSTEARIC ACID (2300 MW); CITRIC ACID MONOHYDRATE; BENZYLIDENE DIMETHOXYDIMETHYLINDANONE

Solar Stick™ Tinted SPF 40
Tinted Broad Spectrum SPF 40 Water Resistant (80 min) Mineral Sunscreen

Drug Facts

ACTIVE INGREDIENT

Active ingredients | Purpose
Titanium Dioxide 8.1% | Sunscreen
Zinc Oxide 6% | Sunscreen

Uses

- Helps prevent sunburn
- If used as directed with other sun protection measures (see Directions), decreases the risk of skin cancer and early skin aging caused by the sun.

Warnings

For external use only

Do not useon damaged or broken skin

Stop use and ask a doctorif rash occurs

WHEN USING

When using this productkeep out of eyes. Rinse with water to remove.

Keep out of reach of children.

If swallowed, get medical help or contact a Poison Control Center right away.

Directions

- Apply liberally 15 minutes before sun exposure
- Reapply:
  - after 80 minutes of swimming or sweating
  - immediately after towel drying
  - at least every 2 hours
- Children under 6 months: Ask a doctor
- Sun Protection Measures:Spending time in the sun increases your risk of skin cancer and early skin aging. To decrease the risk, regularly use a sunscreen with Broad Spectrum SPF of 15 or higher and other sun protection measures including:
  - Limit time in the sun, especially from 10a.m.- 2p.m.
  - Wear long-sleeved shirts, pants, hats and sunglasses

Other Information

Rub in well.

- Protect the product in this container from excessive heat and direct sunlight
- May stain some fabrics
- You may report serious adverse reactions to: Report Reaction LLC PO Box 611, Pompton Plains, NJ 07444

Inactive Ingredients

Polyethylene, Dimethicone, Butyloctyl Salicylate, Petrolatum, Butyrospermum Parkii (Shea) Butter, C12-15 Alkyl Benzoate, Caprylic/Capric Triglyceride, Methyl Dihydroabietate, Acrylates/ Ethylhexyl Acrylate/Dimethicone Methacrylate Copolymer, Octyldodecanol, Tetrahexyldecyl Ascorbate (Vitamin C), Tocopherol (Vitamin E), Behenyl Olivate, Aluminum Hydroxide, Stearic Acid, Sorbitan Sesquioleate, Glyceryl Isostearate, Polyhydroxystearic Acid, Citric Acid, Benzylidene Dimethoxydimethylindanone, May contain: (CI 77491, CI 77494, CI 77499)

DISTRIBUTED BY
MDSOLARSCIENCES CORP.
GREENS FARMS, CT 06838

PRINCIPAL DISPLAY PANEL - 17 G Tube Carton

MDSOLARSCIENCES®

SOLAR STICK™

Tinted Broad Spectrum SPF 40
Water Resistant (80 Min)
Mineral Sunscreen

SPF
40

TINTED

Sheer, lightweight
portable protection

DERMATOLOGIST DEVELOPED
With Vitamins C + E

0.6 OZ / 17 G